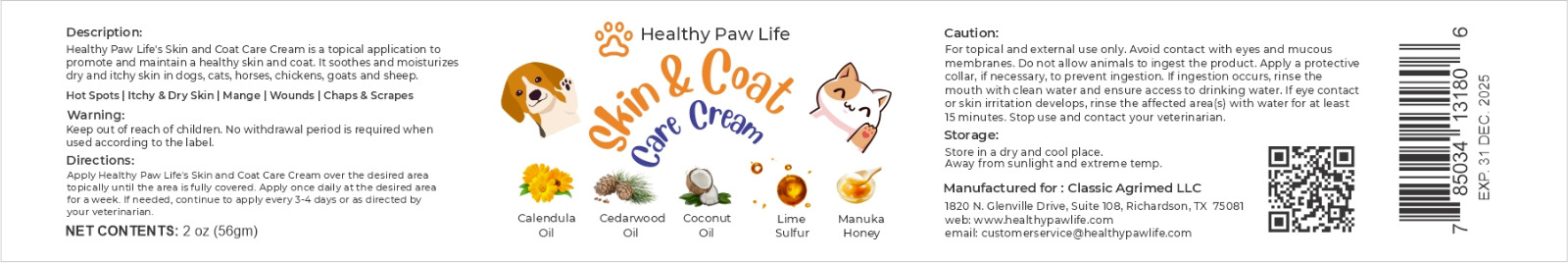 DRUG LABEL: CALENDULA MANUKA HONEY CEDARWOOD
NDC: 86130-901 | Form: CREAM
Manufacturer: CLASSIC AGRIMED LLC
Category: animal | Type: OTC ANIMAL DRUG LABEL
Date: 20231112

ACTIVE INGREDIENTS: CALCIUM POLYSULFIDE 0.11 g/100 g; CALENDULA OFFICINALIS SEED OIL 0.5 g/100 g; CEDAR LEAF OIL 0.2 g/100 g

CALENDULA MANUKA HONEY CEDARWOOD COCONUT LIME SULFUR

Description

Healthy Paw Life's Skin and Coat Care Cream is a topical application to promote and maintain healthy skin and coat. It soothes and moisturizes dry and itchy skin in dogs, cats, horses, chickens, goats and sheep.

Hot Spots | Itchy & Dry Skin | Mange | Wounds | Chaps & Scrapes

Warning:

Keep out of reach of children. No withdrawal period is required when used according to the label.

Directions:

Apply Healthy Paw Life's Skin and Coat Care Cream over the desired area topically until the area is fully covered. Apply once daily at the desired area for a week. If needed, continue to apply every 3-4 days or as directed by your veterinarian.

Caution:

For topical and external use only. Avoid contact with eyes and mucous membranes. Do not allow animals to ingest the product. Apply a protective collar, if necessary, to prevent ingestion. If ingestion occurs, rinse the mouth with clean water and ensure access to drinking water. If eye contact or skin irritiation develops, rinse the affected area(s) with water for at least 15 minutes. Stop use and contact your veterinarian.

Storage:

Store in a dry and cool place. Away from sunlight and extreme temp.